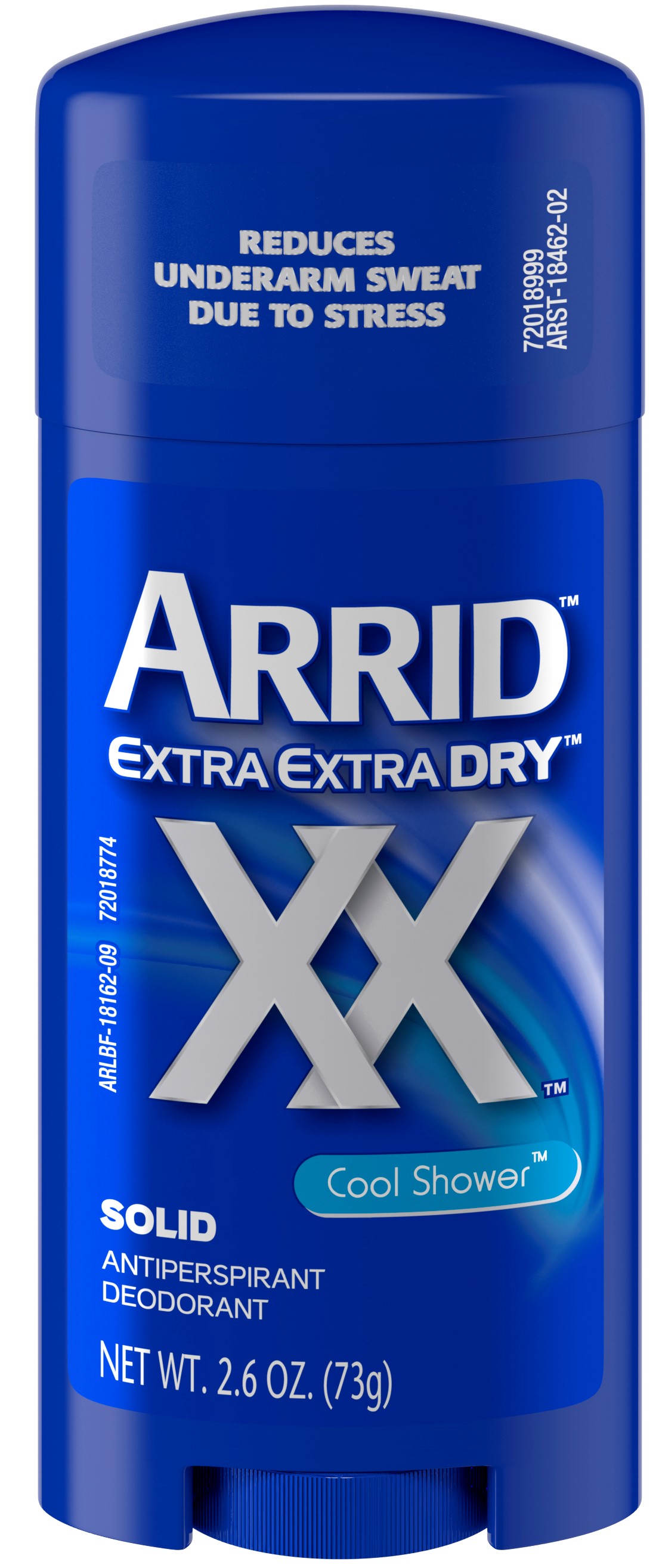 DRUG LABEL: Arrid Extra Extra Dry - Cool Shower
NDC: 10237-867 | Form: STICK
Manufacturer: Church & Dwight Co., Inc.
Category: otc | Type: HUMAN OTC DRUG LABEL
Date: 20241120

ACTIVE INGREDIENTS: ALUMINUM CHLOROHYDRATE 0.19 g/1 g
INACTIVE INGREDIENTS: PPG-14 BUTYL ETHER; CYCLOMETHICONE 5; STEARYL ALCOHOL; C12-20 ALKYL BENZOATE; TALC; HYDROGENATED CASTOR OIL; PETROLATUM; LAURETH-4; FD&C BLUE NO. 1

Arrid Extra Extra Dry - Cool Shower

ACTIVE INGREDIENT

Aluminum Chlorohydrate 19%

PURPOSE

Antiperspirant

INDICATIONS AND USAGE

Usereduces underarm perspiration

WARNINGS

For external use only

Do not useon broken skin

Stop use ifrash or irritation occurs

Ask a doctor before use if you havekidney disease

Keep out of reach of children.If swallowed, get medical help or contact a Poison Control Center right away.

Directions

Apply a thin layer to underarms only

INACTIVE INGREDIENT

PPG-14 Butyl Ether, Cyclopentasiloxane, Stearyl Alcohol, C12-15 Alkyl Benzoate, Talc, Hydrogenated Castor Oil, Petrolatum, Fragrance, Laureth-4, Blue 1.

QUESTIONS

? 1-800-248-8820 M-F 9-5 ET

PACKAGE LABEL

REDUCES

UNDERARM SWEAT

DUE TO STRESS

ARRID

EXTRA EXTRA DRY

XX

Cool Shower

SOLID

ANTIPERSPIRANT

DEODORANT

NET WT. 2.6 OZ. (73g)